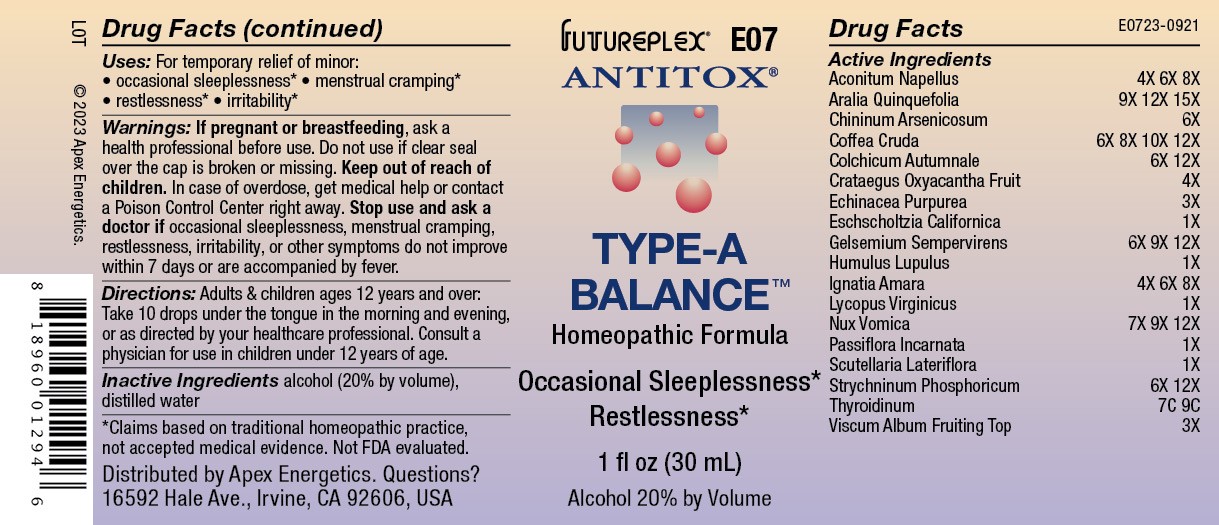 DRUG LABEL: E07
NDC: 63479-0507 | Form: SOLUTION/ DROPS
Manufacturer: Apex Energetics Inc.
Category: homeopathic | Type: HUMAN OTC DRUG LABEL
Date: 20240109

ACTIVE INGREDIENTS: STRYCHNOS IGNATII SEED 8 [hp_X]/1 mL; LYCOPUS VIRGINICUS 1 [hp_X]/1 mL; PASSIFLORA INCARNATA TOP 1 [hp_X]/1 mL; SCUTELLARIA LATERIFLORA WHOLE 1 [hp_X]/1 mL; CRATAEGUS LAEVIGATA FRUIT 4 [hp_X]/1 mL; COLCHICUM AUTUMNALE BULB 12 [hp_X]/1 mL; ARABICA COFFEE BEAN 12 [hp_X]/1 mL; QUININE ARSENITE 6 [hp_X]/1 mL; AMERICAN GINSENG 15 [hp_X]/1 mL; ACONITUM NAPELLUS 8 [hp_X]/1 mL; STRYCHNOS NUX-VOMICA SEED 12 [hp_X]/1 mL; THYROID, UNSPECIFIED 9 [hp_C]/1 mL; STRYCHNINE PHOSPHATE DIHYDRATE 12 [hp_X]/1 mL; VISCUM ALBUM FRUITING TOP 3 [hp_X]/1 mL; GELSEMIUM SEMPERVIRENS ROOT 12 [hp_X]/1 mL; ECHINACEA PURPUREA 3 [hp_X]/1 mL; ESCHSCHOLZIA CALIFORNICA 1 [hp_X]/1 mL; HOPS 1 [hp_X]/1 mL
INACTIVE INGREDIENTS: ALCOHOL; WATER

E07

Active Ingredients
Aconitum napellus | 4X 6X 8X
Aralia quinquefolia | 9X 12X 15X
Chininum arsenicosum | 6X
Coffea cruda | 6X 8X 10X 12X
Colchicum autumnale | 6X 12X
Crataegus oxyacantha fruit | 4X
Echinacea purpurea | 3X
Eschscholtzia californica | 1X
Gelsemium sempervirens | 6X 9X 12X
Humulus lupulus | 1X
Ignatia amara | 4X 6X 8X
Lycopus virginicus | 1X
Nux vomica | 7X 9X 12X
Passiflora incarnata | 1X
Scutellaria lateriflora | 1X
Strychninum phosphoricum | 6X 12X
Thyroidinum | 7C 9C
Viscum album fruiting top | 3X

INDICATIONS AND USAGE

Uses:

For temporary relief of minor:

occasional sleeplessness*

menstrual cramping*
restlessness*

irritability*

*Claims based on traditional homeopathic practice, not accepted medical evidence. Not FDA evaluated.

WARNINGS

PREGNANCY OR BREAST FEEDING

If pregnant or breastfeeding, ask a health professional before use.

Do not use if clear seal over the cap is broken or missing.

Keep out of reach of children. In case of overdose, get medical help or contact a Poison Control Center right away.

Stop use and ask a doctor if occasional sleeplessness, menstrual cramping, restlessness, irritability, or other symptoms do not improve within 7 days or are accompanied by fever.

Directions:

Adults & children ages 12 years and over: Take 10 drops under the tongue in the morning and evening, or as directed by your healthcare professional. Consult a physician for use in children under 12 years of age.

Inactive Ingredients

alcohol (20% by volume), distilled water

Distributed by Apex Energetics. Questions?

16592 Hale Ave., Irvine, CA 92606, USA

PACKAGE LABEL

FUTUREPLEX® E07

ANTITOX®

TYPE-A BALANCE™

Homeopathic Formula

Occasional Sleeplessness*

Restlessness*

1 fl oz (30 mL)

Alcohol 20% by Volume